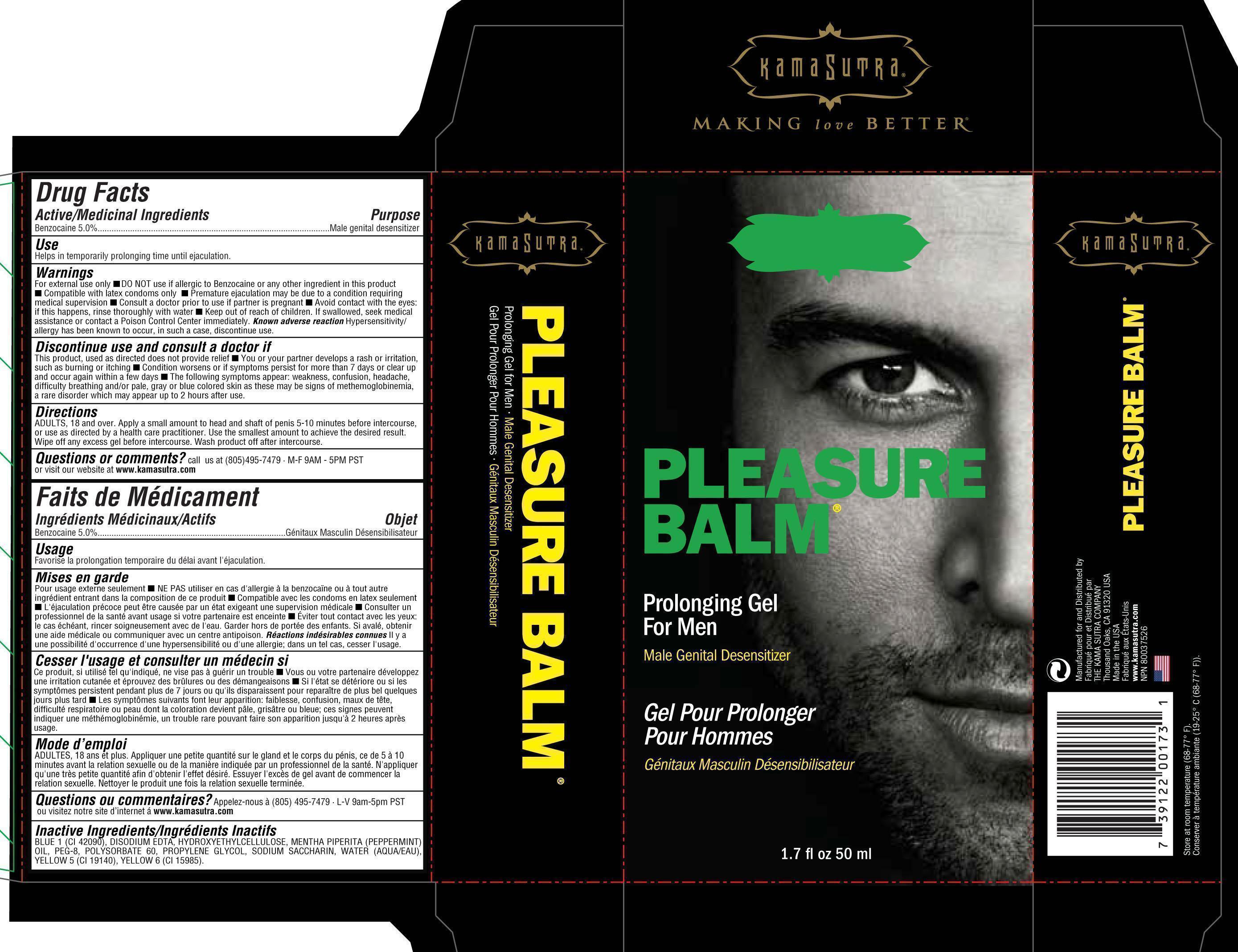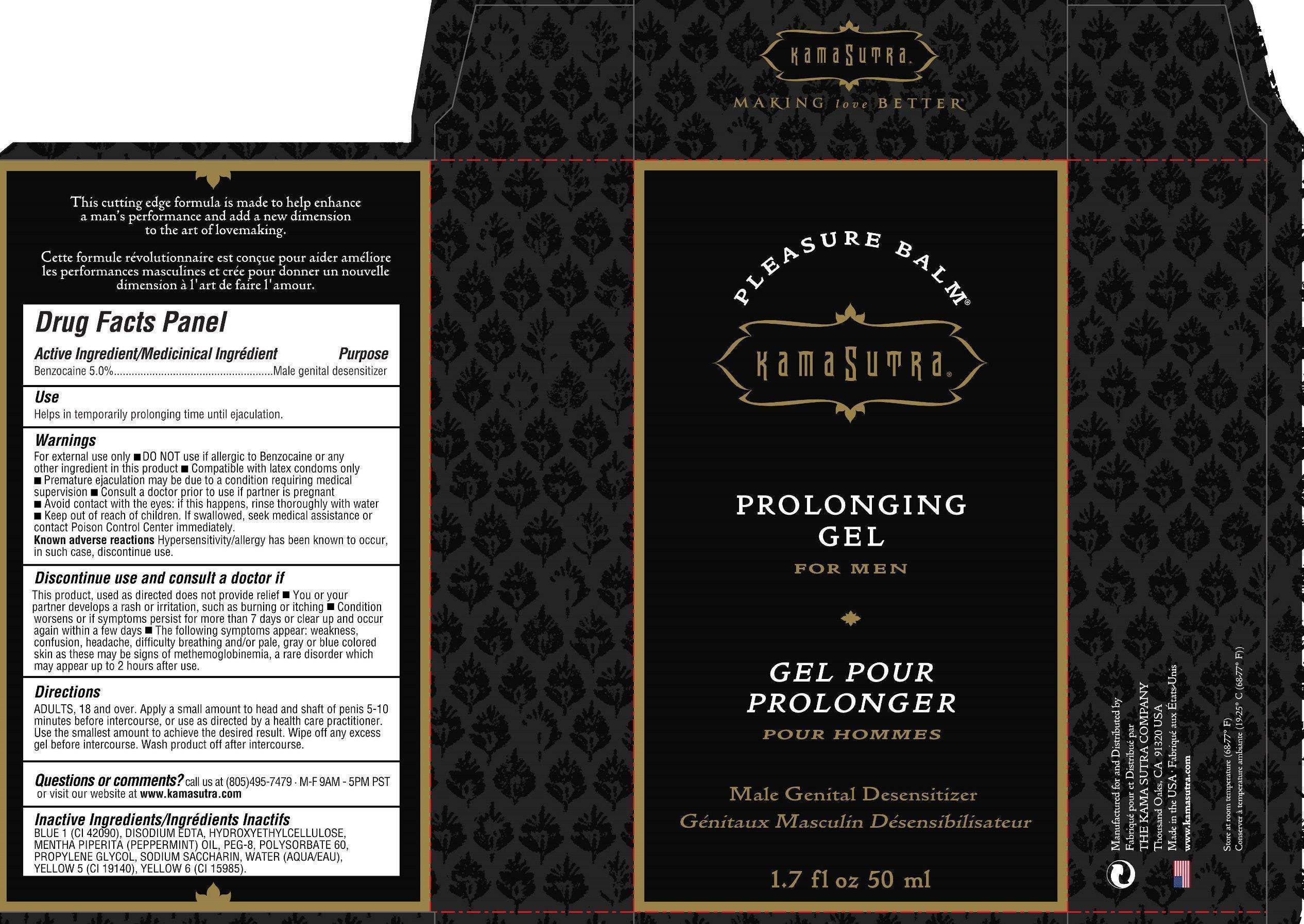 DRUG LABEL: Pleasure Balm
NDC: 75956-147 | Form: GEL
Manufacturer: Kama Sutra
Category: otc | Type: HUMAN OTC DRUG LABEL
Date: 20150115

ACTIVE INGREDIENTS: BENZOCAINE 5 g/100 mL
INACTIVE INGREDIENTS: FD&C BLUE NO. 1; EDETATE DISODIUM; CETYL HYDROXYETHYLCELLULOSE (350000 MW); MENTHA PIPERITA; POLYETHYLENE GLYCOL 400; POLYSORBATE 60; PROPYLENE GLYCOL; SACCHARIN SODIUM; WATER; FD&C YELLOW NO. 5; FD&C YELLOW NO. 6

Pleasure Balm

Active Ingredients Purpose

Benzocaine 5.0 % Male genital desensitizer

Use

Helps in temporarily prolonging time until ejaculation

Keep out of reach of children. If swallowed, seek medical assistance or contact a Poison Control Center immediately.

INDICATIONS AND USAGE

Discontinue use and consult a doctor if

This product, used as directed does not provide relief

You or your partner develops a rash or irritation, such as burning or itching

Condition worsens or if symptoms persist for more than 7 days or clear up and occur again within a few days

The following symptoms appear: weakness, confusion, headache, difficulty breathing and/or pale, gray or blue colored skin as these may be signs of methemoglobinemia

Warnings

For external use only

Do not useif allergic to Benzocaine or any other ingredient in this product

Safe to use only with latex condoms only

Premature ejaculation may be due to condition requiring medical supervision

Consult a doctor prior to use if partner is pregnant

Avoid contact with eyes: if this happens, rinse thoroughly with water

Known adverse reactions Hypersensitivity/allergy has been known to occur, in such a case, discontinue use.

Directions

Adults, 18 and over. Apply a small amount to head and shaft of penis 5-10 minutes before intercourse, or use as directed by a health care practitioner. Use the smallest amount to achieve the desired result. Wipe off any excess gel before intercourse. Wash product off after intercourse.

INACTIVE INGREDIENT

Inactive Inagredients: Blue 1 (CI 42090), Disodium EDTA, Hydroxyethylcellulose, Mentha Piperita (peppermint oil), PEG-8, Polysorbate 60, Propylene Glycol, Sodium Saccharin, Water (Aqua/Eau), Yellow 5 (CI 19140), Yellow 6 (CI 15985)

PACKAGE LABEL

Kama Sutra

Pleasure Balm

Prolonging Gel for Men

Male Genital Desensitizer

Gel pour Prolonger pour hommes

Genitaux Masculin Desensibilisateur

1.7 fl oz 50 ml